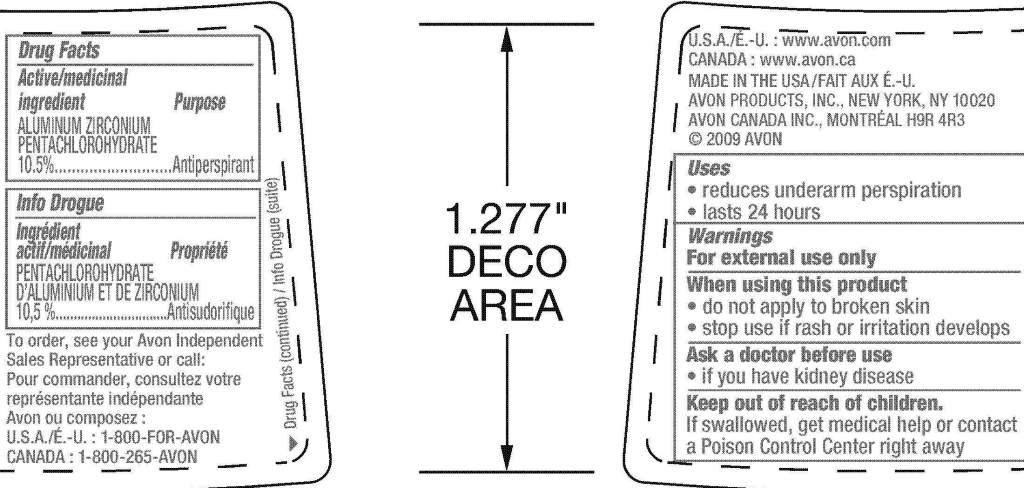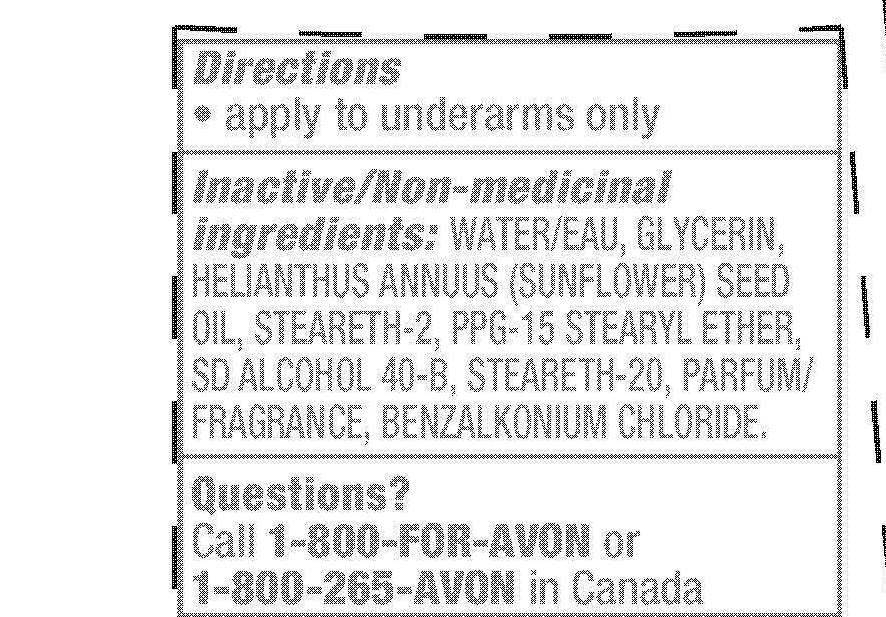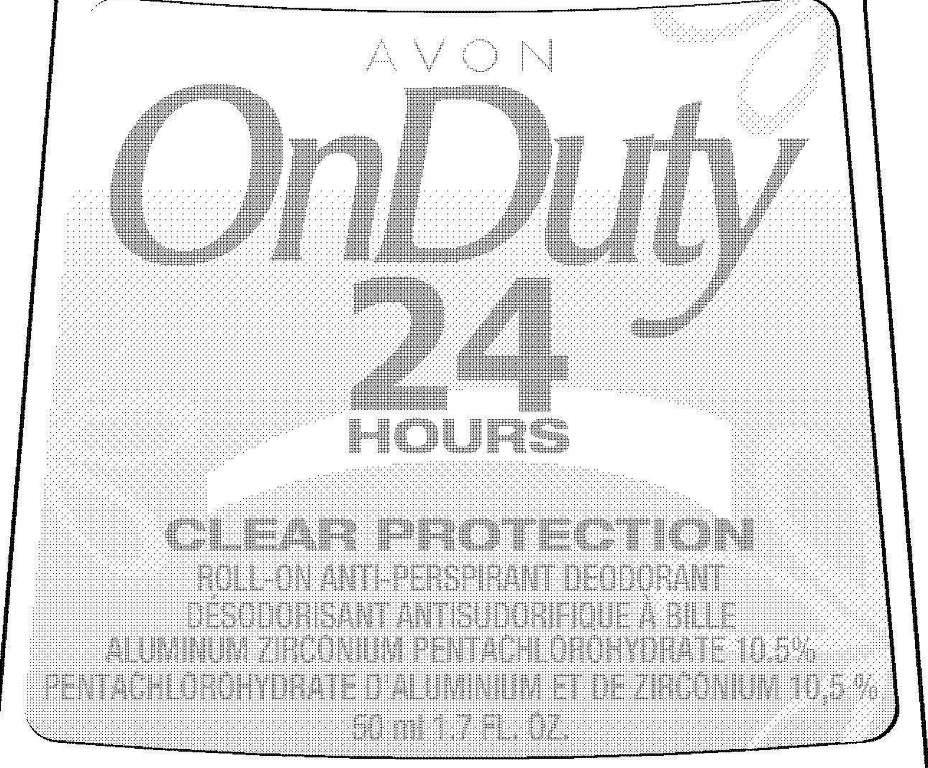 DRUG LABEL: On Duty 24 Hours Clear Protection
NDC: 10096-0243 | Form: GEL
Manufacturer: New Avon LLC
Category: otc | Type: HUMAN OTC DRUG LABEL
Date: 20160216

ACTIVE INGREDIENTS: ALUMINUM ZIRCONIUM PENTACHLOROHYDRATE 105 mg/1 mL

Active/medicinal
ingredient
ALUMINUM ZIRCONIUM
PENTACHLOROHYDRATE
10.5%..............

Purpose
.............Antiperspirant

Uses
• reduces underarm perspiration
• lasts 24 hours

Warnings
For external use only

When using this product
• do not apply to broken skin
• stop use if rash or irritation develops

Ask a doctor before use
• if you have kidney disease

Keep out of reach of children.
If swallowed, get medical help or
contact a Poison Control Center
right away.

Directions
• apply to underarms only

Inactive/Non-medicinal
ingredients: WATER/EAU, GLYCERIN,
HELIANTHUS ANNUUS (SUNFLOWER) SEED
OIL, STEARETH-2, PPG-15 STEARYL ETHER,
SD ALCOHOL 40-B, STEARETH-20, PARFUM/
FRAGRANCE, BENZALKONIUM CHLORIDE.

Questions? Call 1-800-FOR-AVON
or 1-800-265-AVON in Canada